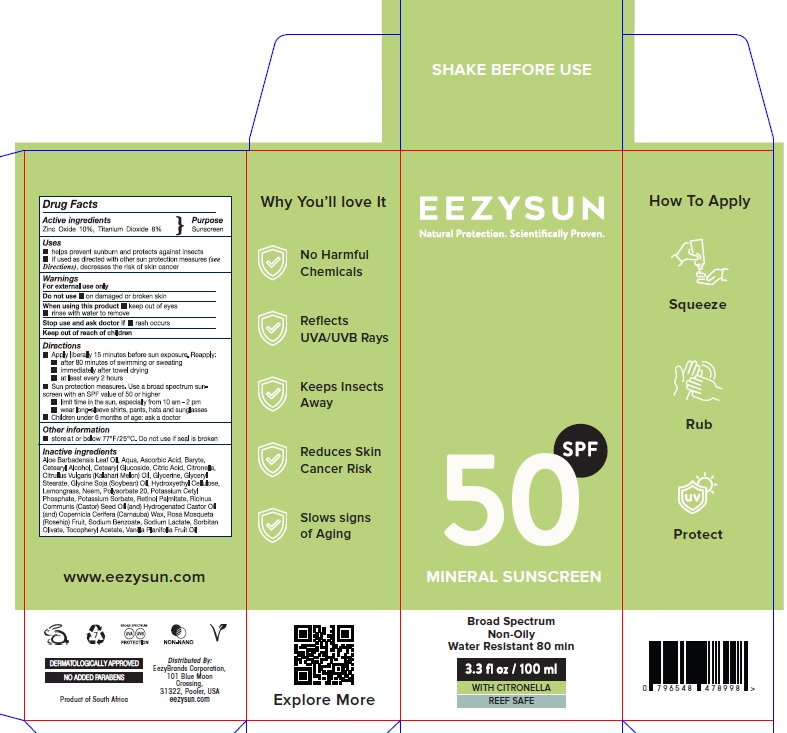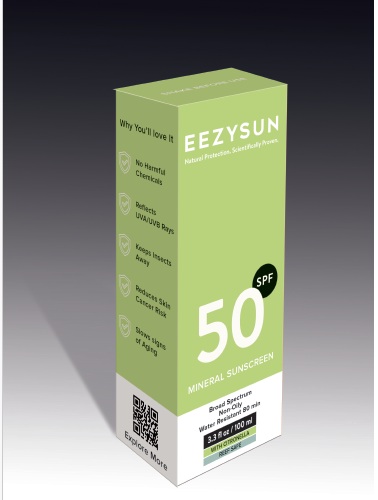 DRUG LABEL: Eezysun SPF 50
NDC: 70116-014 | Form: CREAM
Manufacturer: BIO EARTH MANUFACTURING (PTY) LTD
Category: otc | Type: HUMAN OTC DRUG LABEL
Date: 20250528

ACTIVE INGREDIENTS: TITANIUM DIOXIDE 8 g/100 mL; ZINC OXIDE 10 g/100 mL
INACTIVE INGREDIENTS: ALOE VERA LEAF; WATER; ASCORBIC ACID; BARIUM SULFATE; CETOSTEARYL ALCOHOL; CETEARYL GLUCOSIDE; CITRIC ACID MONOHYDRATE; CITRONELLA OIL; CITRUS X LIMON FLOWERING TOP OIL; GLYCERIN; GLYCERYL MONOSTEARATE; SOYBEAN OIL; HYDROXYETHYL CELLULOSE, UNSPECIFIED; CYMBOPOGON CITRATUS LEAF; AZADIRACHTA INDICA SEED OIL; POLYSORBATE 20; POTASSIUM CETYL PHOSPHATE; POTASSIUM SORBATE; VITAMIN A PALMITATE; CASTOR OIL; HYDROGENATED CASTOR OIL; CARNAUBA WAX; ROSA MOSCHATA OIL; SODIUM BENZOATE; SODIUM LACTATE; .ALPHA.-TOCOPHEROL ACETATE; VANILLA PLANIFOLIA OIL

Active ingredients

Zinc Oxide 10%, Titanium Dioxide 8%

Purpose

Sunscreen

Uses

Helps prevent sunburn and protects against insects
If used as directed with other sun protection measures (See Directions) decreases the risk of skin cancer

Warnings

- For external use only
- Do not useon damaged or broken skin
- When using this productkeep out of eyes ,rinse with water to remove

- Stop use and ask doctor ifrash occurs
- Keep out of reach of children

Direction

- Apply liberally 15 minutes before sun exposure. Reapply:
- after 80 minutes of swimming or sweating
- immediately after towel drying
- at least every 2 hours
- Sun protection measures. Use a broad spectrum sun-screen with an SPF value of 50 or higher
- limit time in the sun, especially from 10 am - 2 pm
- wear long-sleeve shirts, pants, hats and sunglasses
- Children under 6 months of age: ask a doctor

Shake well before use

Other information

store at or below 77°F/25°C . Do not use if seal is broken

Inactive ingredients

Aloe Barbadensis Leaf Oil, Aqua, Ascorbic Acid, Baryte,Cetearyl Alcohol, Cetearyl Glucoside, Citric Acid, Citronella,Citrullus Vulgaris (Kalahari Melon) Oil, Glycerine, Glyceryl Stearate, Glycine Soja (Soybean) Oil, Hydroxyethyl Cellulose,Lemongrass, Neem, Polysorbate 20, Potassium Cetyl
Phosphate, Potassium Sorbate, Retinol Palmitate, Ricinus Communis (Castor) Seed Oil (and) Hydrogenated Castor Oil (and) Copernicia Cerifera (Carnauba) Wax, Rosa Mosqueta (Rosehip) Fruit, Sodium Benzoate, Sodium Lactate, Sorbitan Olivate, Tocopheryl Acetate, Vanilla Planifolia Fruit Oil